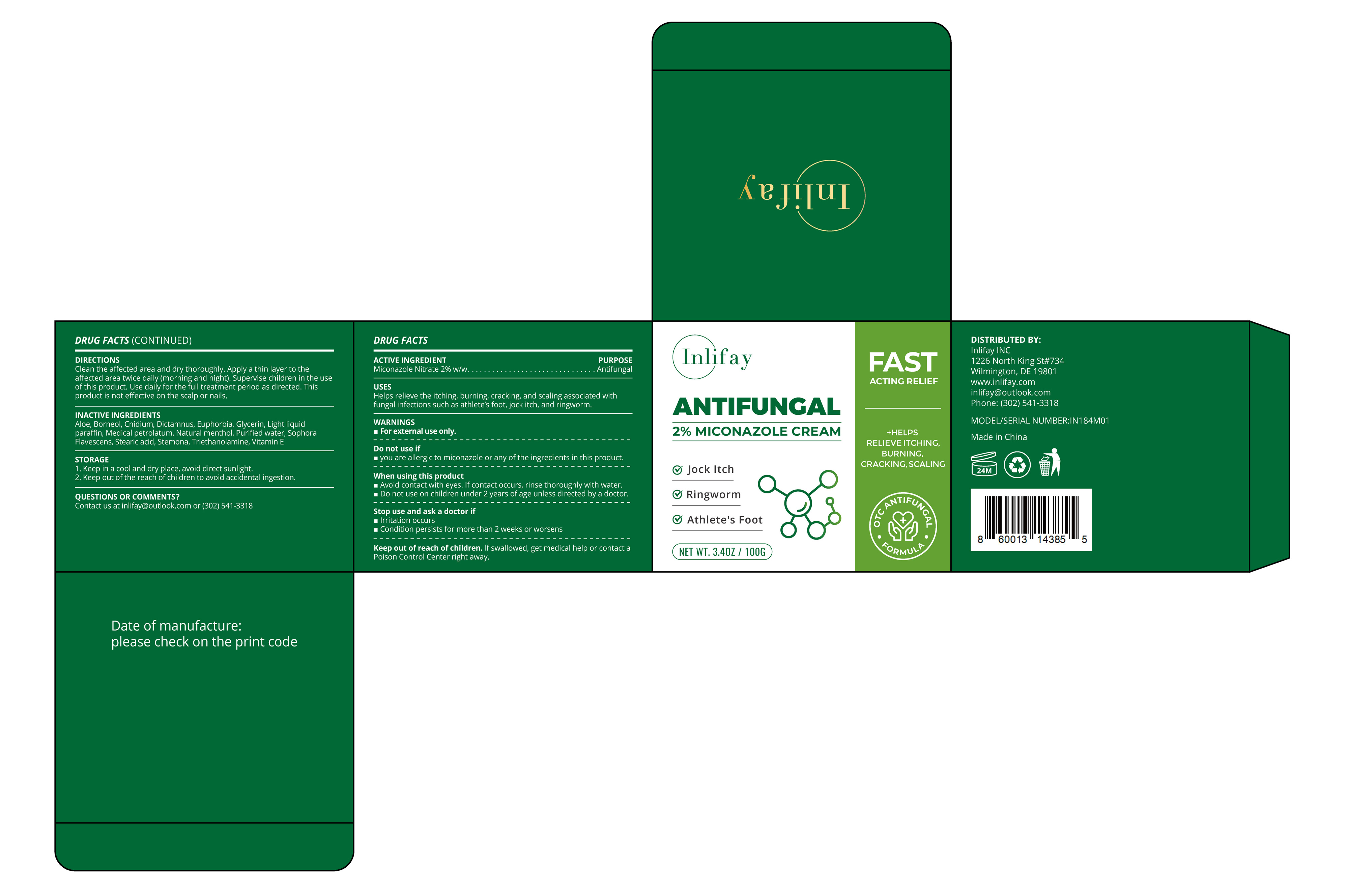 DRUG LABEL: Inlifay  ANTIFUNGAL
NDC: 85248-139 | Form: CREAM
Manufacturer: Jiangxi Yudexi Pharmaceutical Co., LTD
Category: otc | Type: HUMAN OTC DRUG LABEL
Date: 20260210

ACTIVE INGREDIENTS: MICONAZOLE NITRATE 2 g/100 g
INACTIVE INGREDIENTS: TRIETHANOLAMINE; BORNEOL; EUPHORBIA HIRTA; LIGHT MINERAL OIL; LEVOMENTHOL; GLYCERIN; WHITE PETROLATUM; STEMONA TUBEROSA ROOT; STEARIC ACID; WATER; SOPHORA FLAVESCENS ROOT; ALOE

85248-135

Active Ingredient

Miconazole Nitrate 2% w/w

Purpose

Antifungal

Use

Helps relieve the itching, burning, cracking, and scaling associated with fungal infections such as athlete's foot,jock itch, and ringworm.

Warnings

For external use only.

Do not use

you are allergic to miconazole or any of the ingredients in this product

When Using

Avoid contact with eyes. If contact occurs, rinse thoroughly with water.
Do not use on children under 2 years of age unless directed by a doctor.

Stop Use

Irritation occurs Condition persists for more than 2 weeks or worsens

Ask Doctor

Irritation occurs Condition persists for more than 2 weeks or worsens

Keep Oot Of Reach Of Children

If swallowed,get medical help or contact a Poison Control Center right away.

Directions

Clean the affected area and dry thoroughly. Apply a thin layer to the affected area twice daily (morning and night). Supervise children in the use of this product. Use daily for the full treatment period as directed. This product is not effective on the scalp or nails.

Other information

1. Keep in a cool and dry place, avoid direct sunlight. 2. Keep out of the reach of children to avoid accidental ingestion.

Inactive ingredients

Aloe, Borneol, Cnidium, Dictamnus, Euphorbia, Glycerin, Light liquid paraffin, Medical petrolatum, Natural menthol, Purified water, Sophora Flavescens, Stearic acid, Stemona, Triethanolamine, Vitamin E